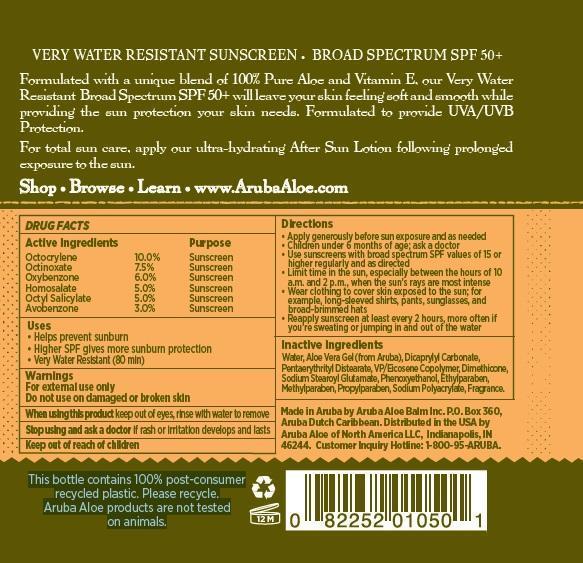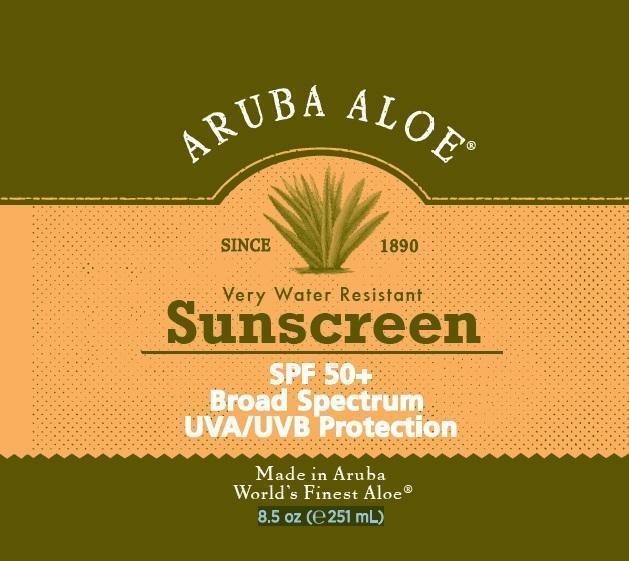 DRUG LABEL: 
                  Aruba Aloe Very Water Resistant Sunscreen

                
                  

NDC: 53675-158 | Form: LOTION
Manufacturer: Aruba Aloe Balm NV
Category: otc | Type: HUMAN OTC DRUG LABEL
Date: 20231106

ACTIVE INGREDIENTS: OCTOCRYLENE 100 mg/1 mL; OCTINOXATE 75 mg/1 mL; OXYBENZONE 60 mg/1 mL; HOMOSALATE 50 mg/1 mL; OCTISALATE 50 mg/1 mL; AVOBENZONE 30 mg/1 mL
INACTIVE INGREDIENTS: WATER; ALOE VERA LEAF; DICAPRYLYL CARBONATE; PENTAERYTHRITYL DISTEARATE; DIMETHICONE; SODIUM STEAROYL GLUTAMATE; PHENOXYETHANOL; ETHYLPARABEN; METHYLPARABEN; PROPYLPARABEN

Very Water Resistant Sunscreen SPF 50+

ACTIVE INGREDIENTS

Octocrylene 10.0% Octinoxate 7.5% Oxybenzone 6.0% Homosalate 5.0% Octyl Salicylate 5.0% Avobenzone 3.0%

PURPOSE

Sunscreen

Uses

• Helps prevent sunburn • Higher SPF gives more sunburn protection • Very Water Resistant (80 min)

Warnings

For external use only Do not use on damaged or broken skin

When using this product

keep out of eyes, rinse with water to remove

Stop using and ask a doctor if

rash or irritation develops and lasts.

Keep out of reach of children.

Directions

- Apply generously before sun exposure and as needed
- Children under 6 months of age; ask a doctor
- Use sunscreens with broad spectrum SPF values of 15 or higher regularly and as directed
- Limit time in the sun, especially between the hours of 10 a.m. and 2 p.m., when the sun’s rays are most intense
- Wear clothing to cover skin exposed to the sun; for example, long-sleeved shirts, pants, sunglasses, and broad-brimmed hats
- Reapply sunscreen at least every 2 hours, more often if you’re sweating or jumping in and out of the water

Inactive Ingredients

Water, Aloe Vera Gel (from Aruba), Dicaprylyl Carbonate, Pentaerythrityl Distearate, VP/Eicosene Copolymer, Dimethicone, Sodium Stearoyl Glutamate, Phenoxyethanol, Ethylparaben, Methylparaben, Propylparaben, Sodium Polyacrylate, Fragrance.

DESCRIPTION

VERY WATER RESISTANT SUNSCREEN • BROAD SPECTRUM SPF 50+

Formulated with a unique blend of 100% Pure Aloe and Vitamin E, our Very Water Resistant Broad Spectrum SPF 50+ will leave your skin feeling soft and smooth while providing the sun protection your skin needs. Formulated to provide UVA/UVB Protection. For total sun care, apply our ultra-hydrating After Sun Lotion following prolonged exposure to the sun

Shop • Browse • Learn • www.ArubaAloe.com

Made in Aruba by Aruba Aloe Balm Inc. P.O. Box 360, Aruba Dutch Caribbean. Distributed in the USA by Aruba Aloe of North America LLC, Indianapolis, IN 46244. Customer Inquiry Hotline: 1-800-95-ARUBA.

This bottle contains 100% post-consumer recycled plastic. Please recycle. Aruba Aloe products are not tested 8.5 oz (251 mL) on animals.